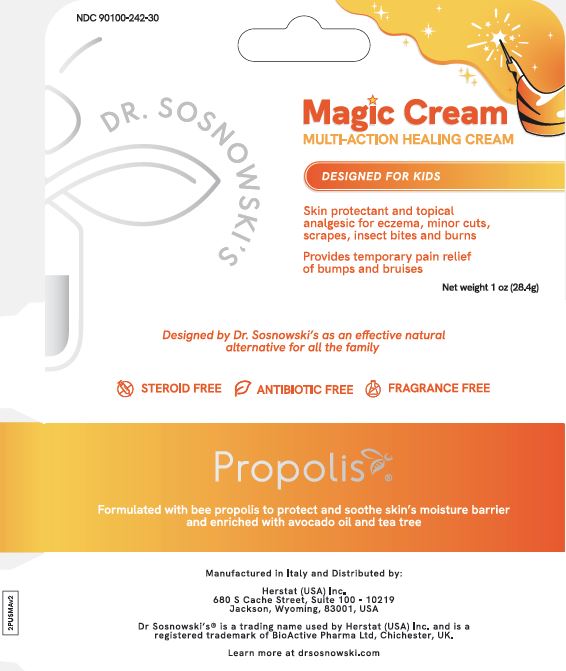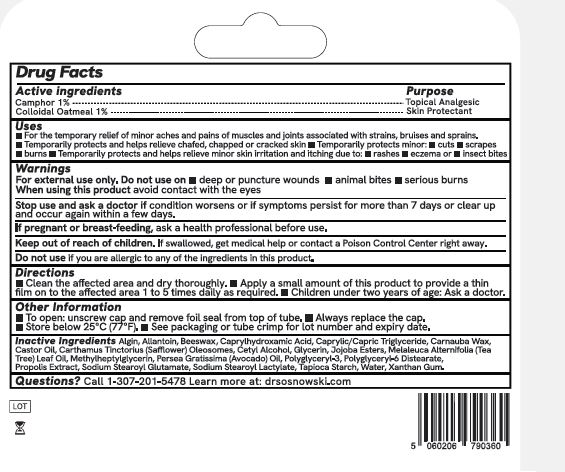 DRUG LABEL: Dr Snosnowskis Magic Healing Cream
NDC: 90100-242 | Form: CREAM
Manufacturer: Herstat (USA) Inc.
Category: otc | Type: HUMAN OTC DRUG LABEL
Date: 20250627

ACTIVE INGREDIENTS: OATMEAL 10 mg/1 g; CAMPHOR (NATURAL) 10 mg/1 g
INACTIVE INGREDIENTS: ALGIN; ALLANTOIN; BEESWAX; CAPRYLHYDROXAMIC ACID; CAPRYLIC/CAPRIC TRIGLYCERIDE; CARNAUBA WAX; RICINUS COMMUNIS (CASTOR) SEED OIL; CARTHAMUS TINCTORIUS (SAFFLOWER) OLEOSOMES; CETYL ALCOHOL; GLYCERIN; HYDROLYZED JOJOBA ESTERS; MELALEUCA ALTERNIFOLIA (TEA TREE) LEAF OIL; GLYCERIN METHYL ETHER; PERSEA GRATISSIMA (AVOCADO) OIL; POLYGLYCERIN-3; POLYGLYCERYL-6 DISTEARATE; PROPOLIS WAX; SODIUM STEAROYL GLUTAMATE; SODIUM STEAROYL LACTYLATE; TAPIOCA STARCH; WATER; XANTHAN GUM

Dr Snosnowskis Magic Healing Cream

Active Ingredient

Camphor 1%

Oatmeal 1%

Purpose

Topical Analgesic

Skin Protectant

Uses:

■ For the temporary relief of minor aches and pains of muscles and joints associated with strains, bruises and sprains.
■ Temporarily protects and helps relieve chafed, chapped or cracked skin ■ Temporarily protects minor: ■ cuts ■ scrapes
■ burns ■ Temporarily protects and helps relieve minor skin irritation and itching due to: ■ rashes ■ eczema or ■ insect bites

Warnings

For external use only. Do not use on ■ deep or puncture wounds ■ animal bites ■ serious burns
When using this product avoid contact with the eyes

Stop use and ask a doctor if condition worsens or if symptoms persist for more than 7 days or clear up and occur again within a few days.

PREGNANCY OR BREAST FEEDING

If pregnant or breast-feeding, ask a health professional before use.

Keep out of reach of children. If swallowed, get medical help or contact a Poison Control Center right away.

Do not use if you are allergic to any of the ingredients in this product.

Directions

■ Clean the affected area and dry thoroughly. ■ Apply a small amount of this product to provide a thin
film on to the affected area 1 to 5 times daily as required. ■ Children under two years of age: Ask a doctor.

Other Information

■ To open: unscrew cap and remove foil seal from top of tube. ■ Always replace the cap.
■ Store below 25ºC (7ºF). ■ See packaging or tube crimp for lot number and expiry date.

Inactive Ingredients:

Inactive Ingredients: Algin, Allantoin, Beeswax, Caprylhydroxamic Acid, Caprylic/Capric Triglyceride, Carnauba Wax,
Castor Oil, Carthamus Tinctorius (Safflower) Oleosomes, Cetyl Alcohol, Glycerin, Jojoba Esters, Melaleuca Alternifolia (Tea
Tree) Leaf Oil, Methylheptylglycerin, Persea Gratissima (Avocado) Oil, Polyglyceryl-3, Polyglyceryl-6 Distearate,
Propolis Extract, Sodium Stearoyl Glutamate, Sodium Stearoyl Lactylate, Tapioca Starch, Water, Xanthan Gum.

Questions?

Questions? Call 1-307-201-5478 Learn more at: drsosnowski.com